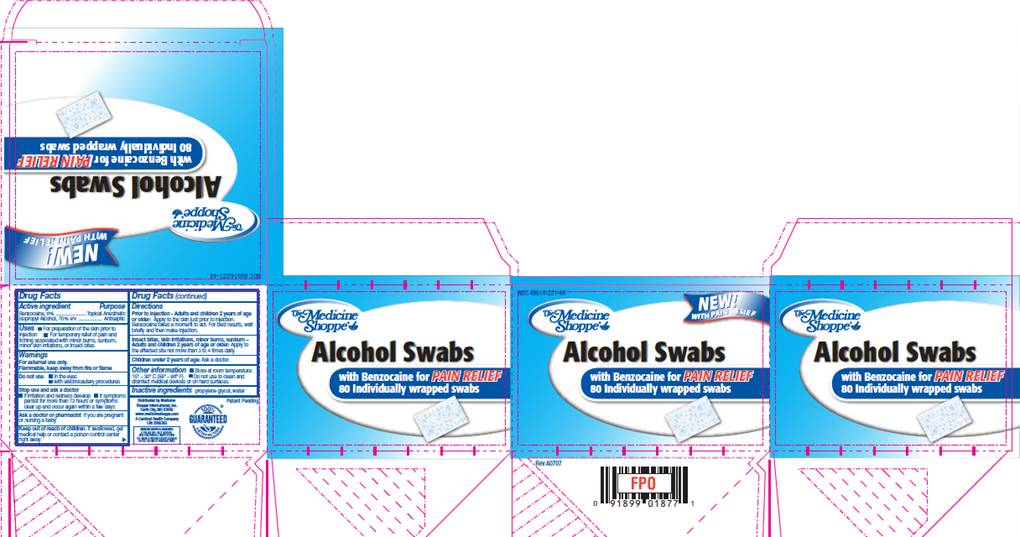 DRUG LABEL: Alcohol Prep Pads with Pain Relief
NDC: 49614-221 | Form: SWAB
Manufacturer: Medicine Shoppe International Inc
Category: otc | Type: HUMAN OTC DRUG LABEL
Date: 20100315

ACTIVE INGREDIENTS: benzocaine 0.06 mL/1 1; isopropyl alcohol 0.70 mL/1 1
INACTIVE INGREDIENTS: propylene glycol; water

DRUG FACTS

ACTIVE INGREDIENTS

Benzocaine 6%
Isopropyl alcohol 70% v/v

PURPOSE

Topical Anesthetic

Antiseptic

USES

- For preparation of the skin prior to injection
- For temporary relief of pain and itching associated with minor burns, sunburn, minor skin irritations, or insect bites

WARNINGS

For external use only.
Flammable, keep away from fire or flame.

Do not use

- in the eyes
- with electrocautery procedures

Stop use and ask a doctor

- if irritation and redness develop
- if symptoms persist for more than 72 hours or symptoms clear up and occur within a few days.

Ask a doctor or pharmacist

if you are pregnant or nursing a baby.

Keep out of reach of children

If swallowed, get medical help or contact a Poison Control Center right away.

DIRECTIONS

Prior to Injection - Adults and children 2 years of age or older:
Apply to the skin just prior to injection. Benzocaine takes a minute to act. for best results, wait briefly and then make injection.
Insect bites, skin irritations, minor burns, sunburn -
Adults and children 2 years of age or older:
Apply to the affected site not more than 3 to 4 times daily.
Children under 2 years of age: Ask a doctor.

OTHER INFORMATION

- Store at room temperature: 15° - 30° C (59° - 86° F)

INACTIVE INGREDIENTS

propylene glycol, water

CARTON INFORMATION

The Medicine Shoppe®

NEW!
WITH PAIN RELIEF

NDC 49614-221-44

Alcohol Swabs
with Benzocaine for PAIN RELIEF

80 Individually wrapped swabs

Distributed by Medicine Shoppe International, Inc.
St. Louis, MO 63162
www.medicineshoppe.com
A Cardinal Health Company;
CIN 3985363
MEDICINE SHOPPE® GUARANTEE
IF YOU ARE NOT FULLY SATISFIED
WITH THIS PRODUCT, SIMPLY RETURN
THE UNUSED PORTION FOR REPLACEMENT
OR FULL REFUND OF PURCHASE PRICE.